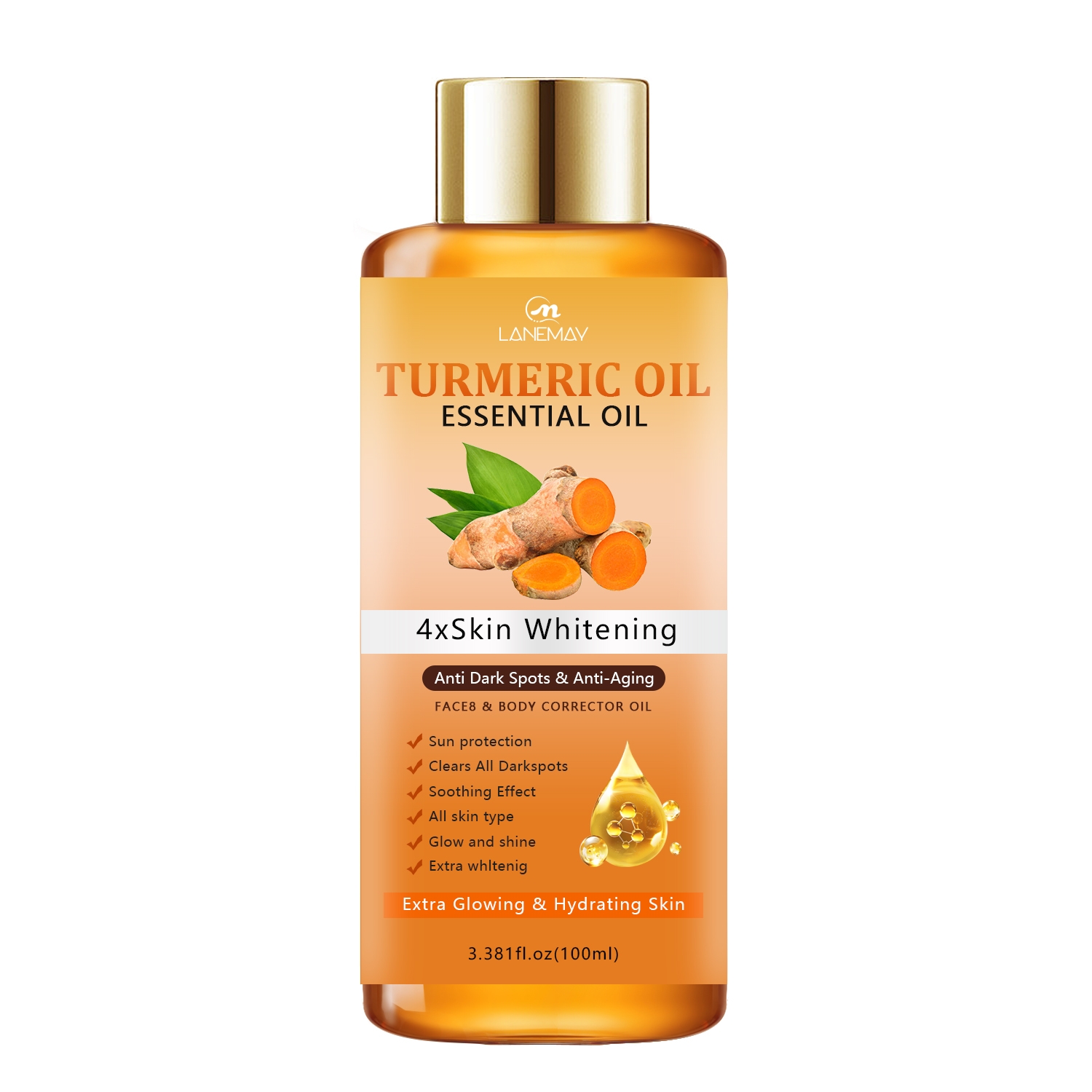 DRUG LABEL: Turmeric Essential Oil
NDC: 84025-208 | Form: OIL
Manufacturer: Guangzhou Yanxi Biotechnology Co., Ltd
Category: otc | Type: HUMAN OTC DRUG LABEL
Date: 20241011

ACTIVE INGREDIENTS: CURCUMIN 5 mg/100 mL
INACTIVE INGREDIENTS: WATER

DOSAGE AND ADMINISTRATION

Use the body oll once per day，apply to clean, dry skin, gently massage the oil onto your skin and continue until most is absorbed.

WARNINGS

keep out of children

INACTIVE INGREDIENT

Aqua

INDICATIONS AND USAGE

For body repair

keep out of children

PURPOSE

Skin moisturizing